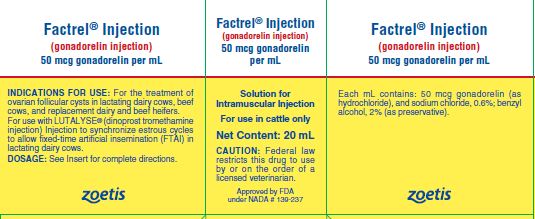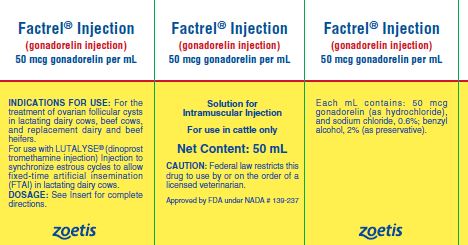 DRUG LABEL: Factrel
NDC: 54771-4311 | Form: INJECTION
Manufacturer: Zoetis Inc.
Category: animal | Type: PRESCRIPTION ANIMAL DRUG LABEL
Date: 20221208

ACTIVE INGREDIENTS: GONADORELIN HYDROCHLORIDE 50 ug/1 mL

Factrel® Injection

Approved by FDA under NADA # 139-237
Factrel® Injection
(gonadorelin injection)
50 mcg gonadorelin per mL (as gonadorelin hydrochloride) Solution for Intramuscular Injection.
For use in cattle only

CAUTION

Federal law restricts this drug to use by or on the order of a licensed veterinarian.

DESCRIPTION

FACTREL Injection is a sterile solution containing 50 micrograms of synthetic gonadorelin (as hydrochloride) per mL in aqueous formulation containing 0.6% sodium chloride and 2% benzyl alcohol (as a preservative).

Gonadorelin is the gonadotropin releasing hormone (GnRH) which is produced by the hypothalamus and causes the release of the gonadotropin luteinizing hormone (LH) and follicle-stimulating hormone (FSH) from the anterior pituitary.

FACTREL Injection has the identical amino acid sequence as endogenous gonadorelin; 5-oxo Pro-His-Trp-Ser-Tyr-Gly-Leu-Arg-Pro-Gly-NH2 with identical physiological activities. The molecular weight of gonadorelin is 1182 with a molecular formula of C55H75N17O13. The corresponding values for gonadorelin hydrochloride are 1219 (1 HCl) expressed as C55H75N17O13HCl, or 1255 (2 HCl) expressed as C55H75N17O13 2HCl.

INDICATIONS FOR USE

For the treatment of ovarian follicular cysts in lactating dairy cows, beef cows, and replacement dairy and beef heifers. The treatment effect of FACTREL Injection when used in lactating dairy cows, beef cows, and replacement dairy and beef heifers is a reduction in the number of days to first estrus.
For use with LUTALYSE® (dinoprost tromethamine injection) Injection to synchronize estrous cycles to allow fixed-time artificial insemination (FTAI) in lactating dairy cows.

DOSAGE

For the treatment of ovarian follicular cysts in lactating dairy cows, beef cows, and replacement dairy and beef heifers: Administer 2 mL of FACTREL Injection as a single intramuscular injection.
For use with LUTALYSE (dinoprost tromethamine injection) Injection to synchronize estrous cycles to allow fixed-time artificial insemination (FTAI) in lactating dairy cows: Administer 2 to 4 mL FACTREL Injection (100-200 mcg gonadorelin) per cow as an intramuscular injection in a treatment regimen with the following framework:
• Administer the first dose of FACTREL Injection (2-4 mL) at Day 0
• Administer LUTALYSE (25 mg dinoprost, as dinoprost tromethamine injection) Injection by intramuscular injection 6-8 days after the first dose of FACTREL Injection.
• Administer a second dose of FACTREL Injection (2-4 mL) 30 to 72 hours after the LUTALYSE injection.
• Perform FTAI 0 to 24 hours after the second dose of FACTREL Injection, or inseminate cows on detected estrus using standard herd practices.

Below are three examples of treatment regimens for FTAI that fit within the dosage regimen framework described immediately above:

 | Example 1 | Example 2 | Example 3
Day 0; (Monday) | 1st FACTREL | 1st FACTREL | 1st FACTREL
Day 7 (the following; Monday) | LUTALYSE | LUTALYSE | LUTALYSE
Day 9; (Wednesday) | 2nd FACTREL + FTAI at; 48 hours after LUTALYSE | 2nd FACTREL; 48 hours after LUTALYSE | 2nd FACTREL; 56 hours after LUTALYSE
Day 10; (Thursday) |  | FTAI; 24 hours after 2nd FACTREL | FTAI; 18 hours after 2nd FACTREL

MECHANISM OF ACTION

Follicular cysts are enlarged non-ovulatory follicles resulting from a malfunction of the neuroendocrine mechanism controlling follicular maturation and ovulation. Exogenous administration of agents possessing luteinizing hormone (LH) activity, such as pituitary extracts or human chorionic gonadotropin, often causes ovulation or regression of follicular cysts. FACTREL Injection induces release of endogenous luteinizing hormone (LH) to produce this same effect.
Gonadorelin, through release of LH has been demonstrated to induce ovulation of dominant ovarian follicles present on the bovine ovary during the estrous cycle. Administration of FACTREL Injection has the same effect.

WARNINGS AND PRECAUTIONS

For use in animals only. Not for human use. Keep out of reach of children.

RESIDUE WARNINGS

No withdrawal period or milk discard time is required when used according to labeling.

EFFECTIVENESS

For the treatment of ovarian follicular cysts in lactating dairy cows, beef cows, and replacement dairy and beef heifers:
The treatment effect of FACTREL Injection when used in lactating dairy cows, beef cows, and replacement dairy and beef heifers is a reduction in the number of days to first estrus.
There were no significant differences in days from treatment to conception, frequency of cows conceiving at first or subsequent heats, or conception rates among treated or non-treated control animals, when FACTREL Injection was used alone for treatment of cystic ovaries.
For use with LUTALYSE (dinoprost tromethamine injection) Injection to synchronize estrous cycles to allow fixed-time artificial insemination (FTAI) in lactating dairy cows:
A field study was conducted to compare control (0 mL FACTREL Injection) to two doses of 2, 3 or 4 mL FACTREL Injection (100-200 mcg gonadorelin) for use with LUTALYSE Injection to synchronize estrous cycles to allow FTAI in lactating dairy cows under field conditions. Cows were examined prior to study start and only clinically normal cows were enrolled. A total of 1142 cows were enrolled at 6 commercial dairies. Cows were assigned randomly in blocks of 4 cows to each of 4 treatment groups consisting of:
Day 0: 2, 3 or 4 mL dose of FACTREL Injection or no injection (Control)
Day 7: 5 mL LUTALYSE Injection (all treatment groups)
Day 9: 2, 3 or 4 mL dose of FACTREL Injection or no injection (Control)
Day 10: Fixed-time artificial insemination

On Day 9 the second dose of FACTREL Injection (cows received the same dose as for first treatment) was given either 48 or 56 hours after the dose of LUTALYSE Injection and FTAI was conducted 24 or 17 hours later, respectively. For control cows FTAI was performed 72 hours after the LUTALYSE Injection dose was administered. All treatment groups had significantly greater pregnancy rates to FTAI than cows administered LUTALYSE Injection alone, and were 17.1, 27.3, 29.1 and 32.2% for cows receiving 0 (Control), 2, 3 or 4 mL FACTREL Injection, respectively.

SAFETY AND TOXICITY

In cows the intramuscular administration of up to 12.5 times maximum recommended dosage (2,500 mcg/day) of FACTREL Injection for 3 days did not affect any physiological or clinical parameter. Likewise, single intramuscular doses of 500 mcg did not interfere with pregnancy. No evidence of irritation at injection site was found in any animal.
A total of 1142 cows were enrolled in the previously noted field study that evaluated the effectiveness of two doses of 2, 3 or 4 mL of FACTREL Injection for use with LUTALYSE Injection to synchronize estrous cycles to allow FTAI in lactating dairy cows. Cows were observed daily for abnormal clinical signs. Over the course of the study there were 148 adverse health events documented in 118 cows. These adverse health events were common conditions in dairy cows (mastitis, lameness and pneumonia) and are not considered related to treatment.

CONTACT INFORMATION

For a copy of the Safety Data Sheet or to report adverse reactions, call Zoetis Inc. at 1-888-963-8471.
For additional information about adverse drug experience reporting for animal drugs, contact FDA at 1-888-FDA-VETS or online at www.fda.gov/reportanimalae.

HOW SUPPLIED

FACTREL Injection (gonadorelin injection), 50 mcg/mL is available in 20 mL and 50 mL multi-dose vials (box of one).

STORAGE CONDITIONS

Store at refrigerator temperature 2° to 8°C (36° to 46°F), with excursions permitted to 25°C (77°F). Use contents within 1 month of first vial puncture.

Approved by FDA under NADA # 139-237
zoetis
Distributed by:
Zoetis Inc.
Kalamazoo, MI 49007
Revised: August 2022
40009636